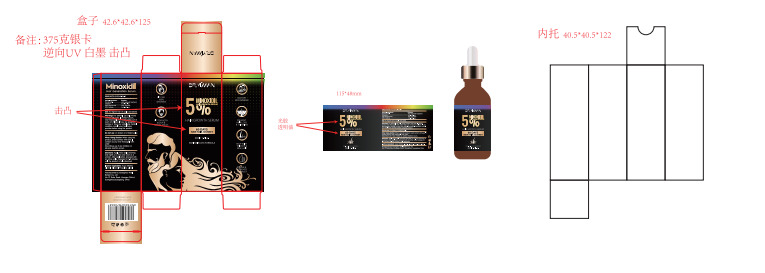 DRUG LABEL: 5% Minoxidil Hair Growth Serum
NDC: 84148-008 | Form: LIQUID
Manufacturer: Guangzhou Ariel Biotech Co., Ltd.
Category: otc | Type: HUMAN OTC DRUG LABEL
Date: 20240923

ACTIVE INGREDIENTS: BIOTIN 0.3 g/100 mL; CAFFEINE 0.2 g/100 mL; NIACINAMIDE 0.2 g/100 mL; MINOXIDIL 5 g/100 mL
INACTIVE INGREDIENTS: WATER; ALCOHOL; PROPYLENE GLYCOL; GLYCERIN

84148-008

Active Ingredient(s)

Minoxidil 5%

Biotin 0.3%

Caffeine 0.2%

Niacinamide 0.2%

Purpose

Hair regrowth treatment
Anti-hair loss
Hair regrowth
Anti- hair loss

Use

Use: To regrow hair of scalp and beard

Warnings

Warnings: For external use only. Avoid contact with eyes. If contact occurs, rinse thoroughly with water. Keep out of reach of
children.lf you are pregnant, nursing, or have any underlying medical condition, consult your healthcare provider before using
the product.

Do not use: on broken or irritated scalp.

WHEN USING

When Using Section: When using this product, avoid contact with eyes. If contact occurs,
rinse thoroughly with water. Discontinve use if any irritation or adverse reaction occurs.

STOP USE

●Scalp iritation or redness occurs.

Keep out of reach of children.

Directions

Directions: Apply twice daily (morning and night) as a man and once as a woman. After application, proceed with an active scalp massage for 3-5 minutes until the product is fully absorbed.

Other information

No Data

Inactive ingredients

Aqua (Water), Alcohol, Glycerol, Propylene glycol